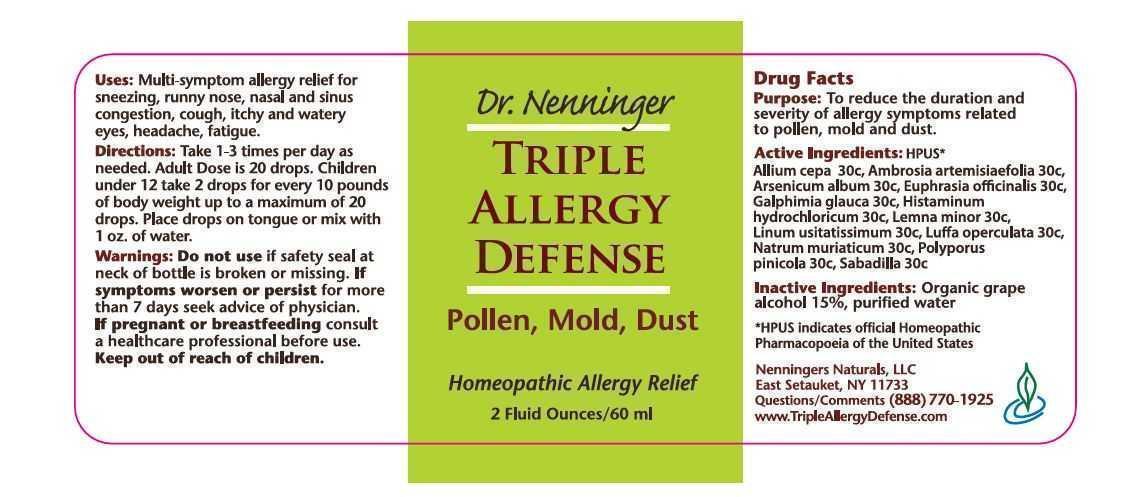 DRUG LABEL: Triple Allergy Defense
NDC: 42731-002 | Form: LIQUID
Manufacturer: Nenningers Naturals, LLC
Category: homeopathic | Type: HUMAN OTC DRUG LABEL
Date: 20130312

ACTIVE INGREDIENTS: ALLIUM CEPA WHOLE 30 [hp_C]/60 mL; AMBROSIA ARTEMISIIFOLIA 30 [hp_C]/60 mL; ARSENIC TRIOXIDE 30 [hp_C]/60 mL; EUPHRASIA STRICTA 30 [hp_C]/60 mL; GALPHIMIA GLAUCA FLOWERING TOP 30 [hp_C]/60 mL; HISTAMINE DIHYDROCHLORIDE 30 [hp_C]/60 mL; LEMNA MINOR 30 [hp_C]/60 mL; FLAX SEED 30 [hp_C]/60 mL; LUFFA OPERCULATA FRUIT 30 [hp_C]/60 mL; SODIUM CHLORIDE 30 [hp_C]/60 mL; FOMITOPSIS PINICOLA FRUITING BODY 30 [hp_C]/60 mL; SCHOENOCAULON OFFICINALE SEED 30 [hp_C]/60 mL
INACTIVE INGREDIENTS: ALCOHOL; WATER

Dr. Nenninger Triple Allergy Defense

Drug Facts

Purpose: To reduce the duration and severity of allergy symptoms related to pollen, mold and dust.

PACKAGE LABEL

Dr. Nenninger

TRIPLE

ALLERGY

DEFENSE

Pollen, Mold, Dust

Homeopathic Allergy Relief

2 Fluid Ounces/60 ml

QUESTIONS

Nenningers Naturals, LLC

East Setauket, NY 11733

Questions/Comments (888) 770-1925

www.TripleAllergyDefense.com

Keep out of reach of children.

WARNINGS

Do not use if safety seal at neck of bottle is broken or missing.

ASK DOCTOR

If symptoms worsen or persist for more than 7 days seek advice from physician.

PREGNANCY OR BREAST FEEDING

If pregnant or breastfeeding consult a healthcare professional before use.

DOSAGE AND ADMINISTRATION

Directions: Take 1-3 times per day as

needed. Adult Dose is 20 drops. Children

under 12 take 2 drops for every 10 pounds

of body weight up to a maximum of 20

drops. Place drops on tongue or mix with

1 oz. of water.

INDICATIONS AND USAGE

Uses: Multi-symptom allergy relief for

sneezing, runny nose, nasal and sinus

congestion, cough, itchy and watery

eyes, headache, fatigue.

Inactive Ingredients: Organic grape

alcohol 15%, purified water

Active Ingredients: HPUS*

Allium cepa 30c, Ambrosia artemisiaefolia 30c,

Arsenicum album 30c, Euphrasia officinalis 30c,

Galphimia glauca 30c, Histaminum

hydrochloricum 30c, Lemna minor 30c,

Linum usitatissimum 30c, Luffa operculata 30c,

Natrum muriaticum 30c, Polyporus

pinicola 30c, Sabadilla 30c

*HPUS indicates official Homeopathic

Pharmacopeia of the United States